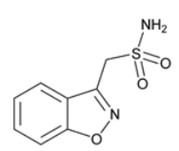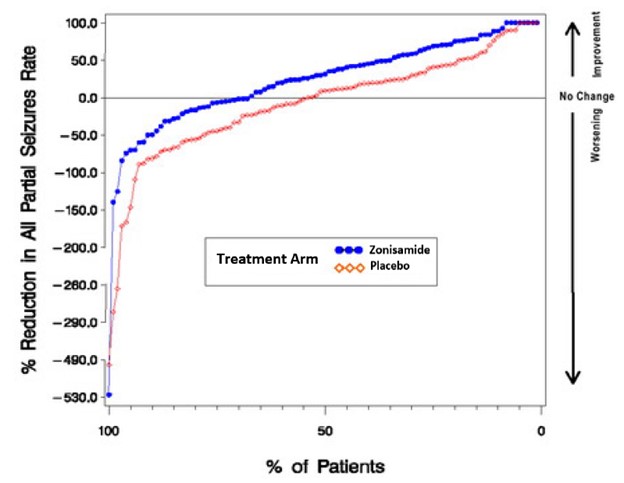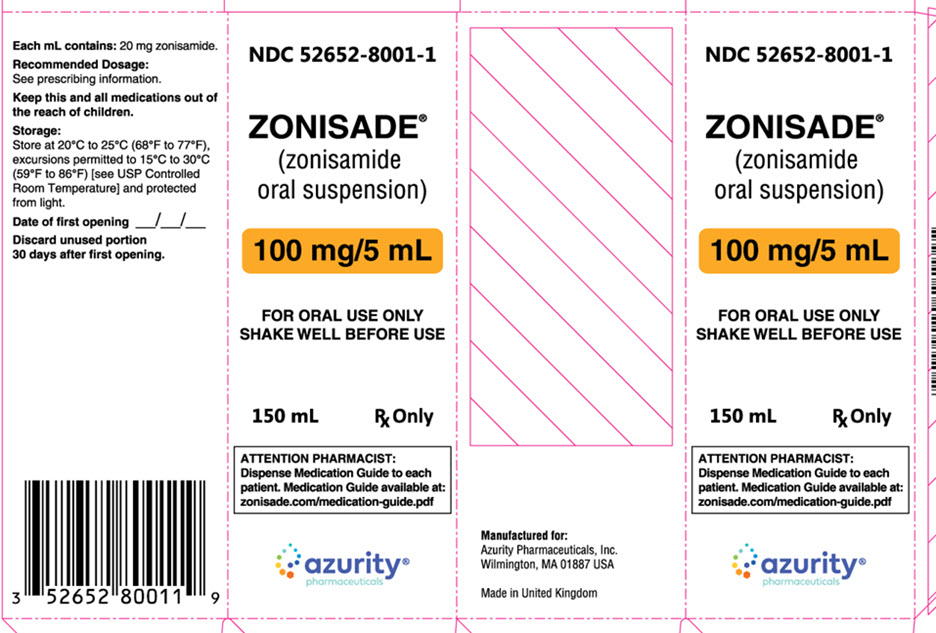 DRUG LABEL: ZONISADE
NDC: 59368-407 | Form: SUSPENSION
Manufacturer: Praxis, LLC
Category: prescription | Type: HUMAN PRESCRIPTION DRUG LABEL
Date: 20230101

ACTIVE INGREDIENTS: ZONISAMIDE 100 mg/5 mL
INACTIVE INGREDIENTS: CARBOXYMETHYLCELLULOSE SODIUM, UNSPECIFIED FORM; CITRIC ACID MONOHYDRATE; MICROCRYSTALLINE CELLULOSE; WATER; SODIUM BENZOATE; SUCRALOSE; TRISODIUM CITRATE DIHYDRATE; XANTHAN GUM

ZONISADE®(zonisamide oral suspension)

8 USE IN SPECIFIC POPULATIONS

8.1 Pregnancy

Pregnancy Exposure Registry

There is a pregnancy exposure registry that monitors pregnancy outcomes in women exposed to antiepileptic drugs, such as ZONISADE, during pregnancy. To provide information regarding the effects of in utero exposure to ZONISADE, physicians are advised to recommend that pregnant patients taking ZONISADE enroll in the North American Antiepileptic Drug (NAAED) Pregnancy Registry. This can be done by calling the toll-free number 1-888-233-2334 and must be done by patients themselves. Information on the registry can also be found at the website http://www.aedpregnancyregistry.org/.

Risk Summary

Based on findings from animal studies, ZONISADE may cause fetal harm when administered to a pregnant woman. Zonisamide causes metabolic acidosis in humans [see Warnings and Precautions (5.8)] . There are no reports of metabolic acidosis with use of zonisamide in pregnancy; however, there are published prospective cohort studies that suggest an increased rate of small for gestational age infants in pregnancies exposed to zonisamide, which may be associated with metabolic acidosis (see Clinical Considerations and Data).

The available published data from the NAAED Pregnancy Registry has not identified a drug-associated risk of major birth defects with zonisamide use in pregnancy. Although a small prospective cohort study reported an increased risk of major birth defects in zonisamide-exposed pregnancies, this study has methodologic limitations, including small sample size and inability to account for potential confounders (see Data).The available published data pertaining to the use of zonisamide during pregnancy are insufficient to evaluate for a drug-associated risk of miscarriage.

In animal studies, administration of zonisamide during pregnancy produced fetal malformations in multiple species and embryofetal (monkey) or perinatal (rat) death at maternal plasma levels similar to or lower than therapeutic levels in humans [see Warnings and Precautions (5.10) and Data].

The estimated background risk of major birth defects and miscarriage for the indicated population is unknown. All pregnancies have a background risk of birth defect, loss, or other adverse outcomes. In the general U.S. population, the estimated background risk of major birth defects and miscarriage in clinically recognized pregnancies is 2-4% and 15-20%, respectively.

Clinical Considerations

Dose Adjustments During Pregnancy and the Postpartum Period

As with other AEDs, physiological changes during pregnancy may affect zonisamide concentrations and/or therapeutic effect. There have been reports of decreased zonisamide concentrations during pregnancy and restoration of pre-pregnancy concentrations after delivery. Dose adjustments may be necessary to maintain clinical response.

Maternal Adverse Reactions

Metabolic acidosis in pregnancy (due to other causes) may be associated with decreased fetal growth, decreased fetal oxygenation, and fetal death, and may affect the fetus' ability to tolerate labor. There are no reports of metabolic acidosis or fetal death with use of zonisamide in pregnancy [see Warnings and Precautions (5.8)] .

Fetal/Neonatal Adverse Reactions

Newborns of mothers treated with zonisamide should be monitored for metabolic acidosis because of transfer of zonisamide to the fetus and possible occurrence of transient metabolic acidosis following birth. Transient metabolic acidosis has been reported in neonates born to mothers treated during pregnancy with a different carbonic anhydrase inhibitor.

Data

Human Data

A prospective cohort study from the NAAED Pregnancy Registry has not identified an increase in the rate of major birth defects (1.4%) in over 200 first trimester pregnancies exposed to zonisamide monotherapy use. Methodological limitations include small sample size and selection bias.

A prospective cohort study from the United Kingdom and Ireland Epilepsy Pregnancy Registry (UKIEPR) reported an increased rate of major birth defects (13%) in 26 first trimester pregnancies exposed to zonisamide monotherapy use. Methodological limitations include small sample size and inability to account for potential confounders.

Prospective cohort studies, including data from NAAED Pregnancy Registry and UKIEPR, have reported increased rates of small for gestational age infants in those exposed to zonisamide during pregnancy compared to lamotrigine-exposed pregnancies and the unexposed general population.

Animal Data

In mice, treatment of pregnant animals with zonisamide (0, 125, 250, or 500 mg/kg/day) during the period of organogenesis resulted in increased incidences of fetal malformations (skeletal and/or craniofacial defects) at all doses tested. A no-effect dose for adverse effects on embryofetal development in mice was not identified. The lowest dose tested was approximately 1.5 times that in humans at the maximum recommended human dose (MRHD) of 400 mg/day on a mg/m^2basis.

In rats, an increased frequency of malformations (cardiovascular defects) and variations (persistent cords of thymic tissue, decreased skeletal ossification) was observed in the offspring of dams treated with zonisamide (0, 20, 60, or 200 mg/kg/day) throughout organogenesis at all doses. A no-effect dose for adverse effects on embryofetal development in rats was not identified. The lowest dose tested was approximately 0.5 times the MRHD on a mg/m^2basis.

Following administration of zonisamide (0, 10, 30, or 60 mg/kg/day) to pregnant dogs during organogenesis, increased incidences of fetal cardiovascular malformations (ventricular septal defects, cardiomegaly, various valvular and arterial anomalies) were found at doses of 30 mg/kg/day or greater. Cardiovascular malformations were found in approximately 50% of all fetuses exposed to the high dose. Incidences of skeletal malformations were also increased at the high dose, and fetal growth retardation and increased frequencies of skeletal variations were seen at all doses. Plasma levels in pregnant dogs (12 μg/mL) at the low and mid doses tested (10 and 30 mg/kg, respectively) were lower than those in humans at the MRHD; plasma levels at the high dose tested in pregnant dogs were similar to those in humans at the MRHD.

In cynomolgus monkeys, administration of zonisamide (0, 10 or 20 mg/kg/day) to pregnant animals during organogenesis resulted in embryofetal deaths at both doses. The possibility that these deaths were due to malformations cannot be ruled out. A no-effect dose for embryofetal death was not identified. At the low dose tested, peak plasma levels in pregnant monkey were substantially lower than that in humans at the MRHD.

Perinatal death was increased among the offspring of rats treated with zonisamide (0, 10, 30, or 60mg/kg/day) from the latter part of gestation up to weaning at the high dose. The no-effect dose (30 mg/kg/day) for adverse peri- and postnatal developmental effects in rats is less than the MRHD on a body surface area (mg/m^2) basis.

8.2 Lactation

Risk Summary

Zonisamide is readily transferred to human milk, with a reported milk-to-plasma ratio ranging between 0.7 to 0.9 in the published lactation studies. There are no published reports of adverse effects on the breastfed infant exposed to zonisamide during breastfeeding. There are no data on the effect of zonisamide on milk production. Because ZONISADE has been associated with metabolic acidosis in adult and pediatric patients and hyperthermia in pediatric patients, infants exposed to ZONISADE during breastfeeding should be monitored for poor feeding, weight loss, excess sedation, decreased muscle tone, and elevated temperature [see Warnings and Precautions (5.8)] .

The developmental and health benefits of breastfeeding should be considered along with the mother’s clinical need for ZONISADE and any potential adverse effects on the breastfed infant from ZONISADE or from the underlying maternal condition.

8.3 Females and Males of Reproductive Potential

Contraception

Females

Based on animal data, zonisamide can cause fetal harm when administered to a pregnant woman [see Warnings and Precautions (5.10)] . Advise females of reproductive potential to use effective contraception during treatment with ZONISADE and for one month after discontinuation.

Infertility

Females

Based on findings from animal fertility studies, ZONISADE may impair fertility in females [see Nonclinical Toxicology (13.1)] .

8.4 Pediatric Use

Safety and effectiveness of ZONISADE have been established in patients 16 years of age and older by evidence from adequate and well-controlled studies of zonisamide [see Clinical Studies (14)] .

Safety and effectiveness in pediatric patients below the age of 16 have not been established. Acute myopia and secondary angle closure glaucoma have been reported in pediatric patients [see Warnings and Precautions (5.6)] . Cases of oligohidrosis and hyperpyrexia have been reported [see Warnings and Precautions (5.5)] . Zonisamide commonly causes metabolic acidosis in pediatric patients [see Warnings and Precautions (5.8)] . Chronic untreated metabolic acidosis in pediatric patients may cause nephrolithiasis and/or nephrocalcinosis, osteoporosis and/or osteomalacia (potentially resulting in rickets), and may reduce growth rates. A reduction in growth rate may eventually decrease the maximal height achieved. The effect of zonisamide on growth and bone-related sequelae has not been systematically investigated.

8.5 Geriatric Use

Single dose pharmacokinetic parameters are similar in elderly and young healthy volunteers [see Clinical Pharmacology (12.3)] . Clinical studies of zonisamide did not include sufficient numbers of subjects aged 65 and over to determine whether they respond differently from younger subjects. Other reported clinical experience has not identified differences in responses between the elderly and younger patients. In general, dose selection for an elderly patient should be cautious, usually starting at the low end of the dosing range, reflecting the greater frequency of decreased hepatic, renal, or cardiac function, and of concomitant disease or other drug therapy.

8.6 Renal Impairment

ZONISADE is cleared via renal pathway [see Clinical Pharmacology (12.3)] . Patients with renal impairment might require slower titration, and more frequent monitoring is required. Avoid use of ZONISADE in patients with renal failure (estimated GFR < 50 mL/min). ZONISADE should be discontinued in patients who develop acute renal failure or a clinically significant sustained increase in the creatinine/BUN concentration [see Warnings and Precautions (5.14)].

10 OVERDOSAGE

10.1 Human Experience

During zonisamide clinical development, three patients ingested unknown amounts of zonisamide as suicide attempts, and all three were hospitalized with CNS symptoms. One patient became comatose and developed bradycardia, hypotension, and respiratory depression; the zonisamide plasma level was 100.1 μg/mL measured 31 hours post-ingestion. Zonisamide plasma levels fell with a half-life of 57 hours, and the patient became alert five days later.

10.2 Management

No specific antidotes for zonisamide overdosage are available. Following a suspected recent overdose, emesis should be induced or gastric lavage performed with the usual precautions to protect the airway. General supportive care is indicated, including frequent monitoring of vital signs and close observation.

Zonisamide has a long half-life [see Clinical Pharmacology (12.3)]. Due to the low protein binding of zonisamide (40%), renal dialysis may be effective. The effectiveness of renal dialysis as a treatment of overdose has not been formally studied. A poison control center should be contacted for information on the management of ZONISADE overdosage.

11 DESCRIPTION

ZONISADE (zonisamide oral suspension) is chemically classified as a sulfonamide. The active ingredient is zonisamide, 1,2-benzisoxazole-3-methanesulfonamide. The empirical formula is C8H8N2O3S with a molecular weight of 212.23. Zonisamide is a white powder, pKa = 10.2, and is moderately soluble in water (0.80 mg/mL) and 0.1 N HCl (0.50 mg/mL).

The chemical structure is:

ZONISADE is an aqueous white to off-white liquid oral suspension. Each mL contains 20 mg of zonisamide. Inactive ingredients include carboxymethylcellulose sodium, citric acid monohydrate, microcrystalline cellulose, purified water, sodium benzoate, strawberry flavor, sucralose, trisodium citrate dihydrate, and xanthan gum.

12 CLINICAL PHARMACOLOGY

12.1 Mechanism of Action

The precise mechanism(s) by which zonisamide exerts its anticonvulsant effects is unknown. Zonisamide may produce these effects through action at sodium and calcium channels. In vitro pharmacological studies suggest that zonisamide blocks sodium channels and reduces voltage-dependent, transient inward currents (T-type Ca2+ currents), consequently stabilizing neuronal membranes. Other in vitro studies have demonstrated that zonisamide (10–30 µg/mL) suppresses synaptically-driven electrical activity without affecting postsynaptic GABA or glutamate responses (cultured mouse spinal cord neurons) or neuronal or glial uptake of [^3H]-GABA (rat hippocampal slices). Thus, zonisamide does not appear to potentiate the synaptic activity of GABA. Zonisamide is a carbonic anhydrase inhibitor. The contribution of this pharmacological action to the therapeutic effects of zonisamide is unknown.

12.2 Pharmacodynamics

As a carbonic anhydrase inhibitor, ZONISADE may cause metabolic acidosis and may also increase the risks of hyperammonemia and kidney stone formation [see Warnings and Precautions (5.8, 5.13, 5.15) and Drug Interactions (7.2)].

12.3 Pharmacokinetics

Absorption

Following a 100 mg ZONISADE dose in normal volunteers, the time to maximum plasma concentrations (Tmax) occurred within 0.5–5 hours.

Zonisamide pharmacokinetics are dose-proportional in the range of 200 to 400 mg. Once a stable dose is reached, steady state is achieved within 14 days.

Effect of Food

When ZONISADE is administered with food, the zonisamide Tmaxis delayed, occurring at 3.5–7.5 hours, but food has no effect on the bioavailability of zonisamide.

Distribution

The apparent volume of distribution (V/F) of zonisamide is about 1.45 L/kg following a 400 mg oral dose. Zonisamide, at concentrations of 1.0–7.0 mcg/mL, is approximately 40% bound to human plasma proteins. Zonisamide extensively binds to erythrocytes, resulting in an eight-fold higher concentration of zonisamide in red blood cells than in plasma. Protein binding of zonisamide is unaffected in the presence of therapeutic concentrations of phenytoin, phenobarbital, or carbamazepine.

Elimination

The plasma clearance of oral zonisamide is approximately 0.30–0.35 mL/min/kg in patients not receiving enzyme-inducing antiepileptic drugs (AEDs). The clearance of zonisamide is increased to 0.5 mL/min/kg in patients concurrently on enzyme-inducing AEDs (see Potential for Other Drugs to Affect ZONISADE). After a single-dose administration, renal clearance of zonisamide is approximately 3.5 mL/min.

Metabolism

Zonisamide is metabolized by N-acetyl-transferases to form N-acetyl zonisamide and by CYP3A4 to form 2–sulfamoylacetylphenol (SMAP).

Excretion

The elimination half-life of zonisamide in plasma is approximately 63 hours. The elimination half-life of zonisamide in red blood cells is approximately 105 hours. Zonisamide is excreted primarily in urine as parent drug and as the glucuronide of a metabolite. Following multiple dosing, 62% of the radiolabeled dose was recovered in the urine, with 3% in the feces by day 10. Of the excreted dose, 35% was recovered as zonisamide, 15% as N-acetyl zonisamide, and 50% as the glucuronide of SMAP.

Specific Populations

Patients with Renal Impairment

Single 300 mg zonisamide doses were administered to three groups of volunteers. Group 1 was a healthy group with a creatinine clearance ranging from 70–152 mL/min. Group 2 and Group 3 had creatinine clearances ranging from 14.5–59 mL/min and 10–20 mL/min, respectively. Zonisamide renal clearance decreased with decreasing renal function (3.42, 2.50, and 2.23 mL/min, respectively). Marked renal impairment (creatinine clearance < 20 mL/min) was associated with an increase in zonisamide AUC of 35% [see Use in Specific Populations (8.6)] .

Patients with Hepatic Impairment

The pharmacokinetics of zonisamide in patients with impaired liver function have not been studied .

Age

The pharmacokinetics of a 300 mg single dose of zonisamide were similar in young (mean age 28 years) and elderly subjects (mean age 69 years).

Drug Interaction Studies

In-Vitro Studies

Enzymes

In vitro studies using human liver microsomes show insignificant (<25%) inhibition of cytochrome P450 isozymes 1A2, 2A6, 2C9, 2C19, 2D6, 2E1, 3A4, 2B6, or 2C8 at zonisamide levels approximately two-fold or greater than clinically relevant unbound serum concentrations. Therefore, ZONISADE is not expected to affect the pharmacokinetics of other drugs via cytochrome P450-mediated mechanisms.

Transporters

An in-vitrostudy showed that zonisamide is a weak inhibitor of P-gp (MDR1).

In-Vivo Studies

Potential for Zonisamide to Affect Other Drugs

Antiepileptic Drugs

In epileptic patients, steady state dosing with zonisamide capsules resulted in no clinically relevant pharmacokinetic effects on carbamazepine, lamotrigine, phenytoin, or sodium valproate.

Oral Contraceptives

In healthy subjects, steady state dosing with zonisamide capsules did not affect serum concentrations of ethinylestradiol or norethisterone in a combined oral contraceptive.

CYP2D6 Substrates

Coadministration of multiple dosing of zonisamide up to 400 mg/day with single 50-mg doses of desipramine did not significantly affect the pharmacokinetic parameters of desipramine, a probe drug for CYP2D6 activity.

Potential for Other Drugs to Affect ZONISADE

CYP3A4 Inducers

The half-life of zonisamide following a 400 mg dose in patients concurrently on enzyme-inducing AEDs such as phenytoin, carbamazepine, or phenobarbital, was between 27-38 hours; the half-life of zonisamide in patients concurrently on the non-enzyme inducing AED, valproate, was 46 hours.

These effects are unlikely to be of clinical significance when ZONISADE is added to existing therapy; however, changes in zonisamide concentrations may occur if concomitant CYP3A4 inducing antiepileptic or other drugs are withdrawn, dose adjusted or introduced, an adjustment of the ZONISADE dose may be required [see Drug Interactions (7.3)] .

CYP3A4 Inhibitors

Steady-state dosing of either ketoconazole (400 mg/day) or cimetidine (1200 mg/day) had no clinically relevant effects on the single dose pharmacokinetics of zonisamide given to healthy subjects.

13 NONCLINICAL TOXICOLOGY

13.1 Carcinogenicity, Mutagenesis, Impairment of Fertility

Carcinogenicity

No evidence of carcinogenicity was found in mice or rats following dietary administration of zonisamide for two years at doses of up to 80 mg/kg/day. In mice, this dose is approximately equivalent to the maximum recommended human dose (MRHD) of 400 mg/day on a mg/m2 basis. In rats, this dose is 1–2 times the MRHD on a mg/m2 basis.

Mutagenesis

Zonisamide was mutagenic in an in vitro chromosomal aberration assay in CHL cells. Zonisamide was not mutagenic or clastogenic in other in vitro assays (Ames, mouse lymphoma tk assay, chromosomal aberration in human lymphocytes) or in the in vivo rat bone marrow cytogenetics assay.

Impairment of Fertility

Rats treated with zonisamide (20, 60, or 200 mg/kg) before mating and during the initial gestation phase showed signs of reproductive toxicity (decreased corpora lutea, implantations, and live fetuses) at all doses. The low dose in this study is approximately 0.5 times the maximum recommended human dose (MRHD) on a mg/m^2basis.

14 CLINICAL STUDIES

The efficacy of ZONISADE is based upon a bioavailability study comparing ZONISADE oral suspension to zonisamide capsules in healthy subjects. The clinical studies information described below pertains to the zonisamide capsule formulation.

The effectiveness of zonisamide as adjunctive therapy has been established in three multicenter, placebo-controlled, double blind, 3-month clinical trials (two domestic, one European) in 499 patients with refractory partial-onset seizures with or without secondary generalization. Each patient had a history of at least four partial-onset seizures per month in spite of receiving one or two antiepilepsy drugs at therapeutic concentrations. The 499 patients (209 women, 290 men) had a mean age of about 35 years. In the two US studies, over 80% of patients were Caucasian; 100% of patients in the European study were Caucasian. Zonisamide capsules or placebo was added to the existing therapy. The primary measure of effectiveness was median percent reduction from baseline in partial seizure frequency. The secondary measure was proportion of patients achieving a 50% or greater seizure reduction from baseline (responders). The results described below are for all partial seizures in the intent-to-treat populations.

In the first study (n = 203), all patients had a 1-month baseline observation period, then received placebo or zonisamide capsules in one of two dose escalation regimens; either 1) 100 mg/day for five weeks, 200 mg/day for one week, 300 mg/day for one week, and then 400 mg/day for five weeks; or 2) 100 mg/day for one week, followed by 200 mg/day for five weeks, then 300 mg/day for one week, then 400 mg/day for five weeks. This design allowed a 100 mg vs. placebo comparison over weeks 1–5, and a 200 mg vs. placebo comparison over weeks 2–6; the primary comparison was 400 mg (both escalation groups combined) vs. placebo over weeks 8–12. The total daily dose was given as twice a day dosing. Statistically significant treatment differences favoring zonisamide were seen for doses of 100, 200, and 400 mg/day.

In the second (n = 152) and third (n = 138) studies, patients had a 2–3 month baseline, then were randomly assigned to placebo or zonisamide capsules for three months. Zonisamide was introduced by administering 100 mg/day for the first week, 200 mg/day the second week, then 400 mg/day for two weeks, after which the dose could be adjusted as necessary to a maximum dose of 20 mg/kg/day or a maximum plasma level of 40 µg/mL. In the second study, the total daily dose was given as twice a day dosing; in the third study, it was given as a single daily dose. The average final maintenance doses received in the studies were 530 and 430 mg/day in the second and third studies, respectively. Both studies demonstrated statistically significant differences favoring zonisamide for doses of 400–600 mg/day, and there was no apparent difference between once daily and twice daily dosing (in different studies). Analysis of the data (first 4 weeks) during titration demonstrated statistically significant differences favoring zonisamide at doses between 100 and 400 mg/day. The primary comparison in both trials was for any dose over Weeks 5–12.

Table 3. Median % Reduction in All Partial-Onset Seizures and % Responders in Primary Efficacy Analyses: Intent-To-Treat Analysis
Study | Median % Reduction in Partial-Onset Seizures |  | % Responders
 | Zonisamide Capsules | Placebo | Zonisamide Capsules | Placebo
Study 1: | n=98 | n=72 | n=98 | n=72
Weeks 8-12: | 40.5% [p<0.05 compared to placebo] | 9.0% | 41.8% | 22.2%
Study 2: | n=69 | n=72 | n=69 | n=72
Weeks 5-12: | 29.6% | -3.2% | 29.0% | 15.0%
Study 3: | n=67 | n=66 | n=67 | n=66
Weeks 5-12: | 27.2% | -1.1% | 28.0% | 12.0%

Table 4. Median % Reduction in All Partial-Onset Seizures and % Responders for Dose Analyses in Study 1: Intent-To-Treat Analysis
Dose Group | Median % Reduction in Partial-Onset Seizures |  | % Responders
 | Zonisamide Capsules | Placebo | Zonisamide Capsules | Placebo
100-400 mg/day: | n=112 | n=83 | n=112 | n=83
Weeks 1-12: | 32.3% [p<0.05 compared to placebo] | 5.6% | 32.1% | 9.6%
100 mg/day: | n=56 | n=80 | n=56 | n=80
Weeks 1-5: | 24.7% | 8.3% | 25.0% | 11.3%
200 mg/day: | n=55 | n=82 | n=55 | n=82
Weeks 2-6: | 20.4% | 4.0% | 25.5% | 9.8%

In Figure 1, a positive value on the Y-axis indicates an improvement from baseline (i.e., a decrease in seizure rate), while a negative value indicates a worsening from baseline (i.e., an increase in seizure rate). Thus, in a display of this type, the curve for an effective treatment is shifted to the left of the curve for placebo. The proportion of patients achieving any particular level of reduction in seizure rate was consistently higher for the zonisamide groups compared to the placebo groups. For example, Figure 1 indicates that approximately 27% of patients treated with zonisamide experienced a 75% or greater reduction, compared to approximately 12% in the placebo groups.

No differences in efficacy based on age, sex or race, as measured by a change in seizure frequency from baseline, were detected.

16 HOW SUPPLIED/STORAGE AND HANDLING

16.1 How Supplied

ZONISADE (zonisamide oral suspension) is a white to off-white, strawberry flavored liquid containing 100 mg/5 mL zonisamide. It is supplied in a 150 mL amber colored PET bottle with a child resistant cap.

NDC Number: 52652-8001-1

16.2 Storage and Handling

Store at 20°C to 25°C (68°F to 77°F), excursions permitted from 15°C to 30°C (59°F to 86°F) [see USP Controlled Room Temperature]. Protect from light.

Discard unused portion of ZONISADE 30 days after first opening of the bottle.

17 PATIENT COUNSELING INFORMATION

Advise the patient to read the FDA-approved patient labeling (Medication Guide).

Administration

Inform patients that a pharmacist will provide an appropriate device and instructions for measuring the correct dose and that a household teaspoon is not an accurate measuring device. Instruct patients to shake ZONISADE well and discard any unused portion after 30 days of opening the bottle [see Dosage and Administration (2.2)] .

Drowsiness

ZONISADE may produce drowsiness, especially at higher doses. Patients should be advised not to drive a car or operate other complex machinery until they have gained experience on ZONISADE sufficient to determine whether it affects their performance. Because of the potential of zonisamide to cause CNS depression, as well as other cognitive and/or neuropsychiatric adverse events, ZONISADE should be used with caution if used in combination with alcohol or other CNS depressants.

Serious Skin Reactions

Patients should contact their physicians immediately if a skin rash develops [see Warnings and Precautions (5.2)] .

Acute Myopia and Secondary Angle Closure Glaucoma

Instruct patients to seek immediate medical attention if they experience blurred vision, visual disturbances, or periorbital pain [see Warnings and Precautions (5.6)] .

Kidney Stones

Patients should contact their physician immediately if they develop signs or symptoms, such as sudden back pain, abdominal pain, and/or blood in the urine, that could indicate a kidney stone. Increasing fluid intake and urine output may reduce the risk of stone formation, particularly in those with predisposing risk factors for stones [see Warnings and Precautions (5.15)] .

Oligohidrosis and Hyperthermia in Pediatric Patients

Patients should contact their physician immediately if a child has been taking ZONISADE and is not sweating as usual with or without a fever [see Warnings and Precautions (5.5)].

Serious Hematologic Events

Because zonisamide can cause hematological complications, patients should contact their physician immediately if they develop a fever, sore throat, oral ulcers, or easy bruising [see Warnings and Precautions (5.3)].

Suicidal Behavior and Ideation

Counsel patients and caregivers that AEDs, including ZONISADE, may increase the risk of suicidal thoughts and behavior and advise them of the need to be alert for the emergence or worsening of symptoms of depression, any unusual changes in mood or behavior, or the emergence of suicidal thoughts, behavior, or thoughts about self-harm. Behaviors of concern should be reported immediately to healthcare providers [see Warnings and Precautions (5.7)].

Hyperammonemia and Encephalopathy

Warn patients about the possible development of hyperammonemia with or without encephalopathy. Although hyperammonemia may be asymptomatic, clinical symptoms of hyperammonemic encephalopathy often include acute alterations in level of consciousness and/or cognitive function with lethargy and/or vomiting. Instruct patients to contact their physician if they develop unexplained lethargy, vomiting, or changes in mental status [see Warnings and Precautions (5.13)].

Metabolic Acidosis

Patients should contact their physician immediately if they develop fast breathing, fatigue/tiredness, loss of appetite, or irregular heartbeat or palpitations, which are possible manifestations of metabolic acidosis [see Warnings and Precautions (5.8)].

Pregnancy

Advise pregnant women and females of reproductive potential of the risk to a fetus. Advise pregnant women to inform their healthcare provider of a known or suspected pregnancy.

Advise women who are exposed to ZONISADE during pregnancy that there is a pregnancy registry that monitors pregnancy outcomes in women exposed to ZONISADE during pregnancy. Encourage patients to report their pregnancy to North American Antiepileptic Drug (NAAED) Pregnancy Registry at 1-888-233-2334 or http://www.aedpregnancyregistry.org/ [see Use in Specific Populations (8.1)].

Lactation

Advise breastfeeding women using ZONISADE to monitor infants for increased sleepiness, decreased appetite, and elevated temperature and to seek medical attention if they notice these signs [see Use in Specific Populations (8.2)].

Manufactured for:
Azurity Pharmaceuticals, Inc.
Wilmington, MA 01887

Made in United Kingdom

Patent: https://azurity.com/patents

This product’s labeling may have been updated. For current Full Prescribing Information, please visit www.zonisade.com

PN: 65628-00630 REV#: 01 03/23

Medication Guide
ZONISADE®(Zaan-i-said)

(zonisamide oral suspension)

What is the most important information I should know about ZONISADE?

- ZONISADE may cause serious skin reactions that can cause death. These serious skin reactions may include a severe rash with blisters and peeling skin, especially around the mouth, nose, eyes and genitals (Stevens-Johnson syndrome). ZONISADE may also cause a rash with blisters and peeling skin over much of the body (toxic epidermal necrolysis). Call your healthcare provider right away if you develop a skin rash.
- ZONISADE can cause blood cell changes such as reduced red and white blood cell counts.Call your healthcare provider right away if you develop fever, sore throat, sores in your mouth, or easy bruising.
- ZONISADE can cause other types of allergic reactions or serious problems that may affect different parts of the body such as your liver, kidneys, heart, or blood cells.You may or may not have a rash with these types of reactions. These reactions can be very serious and can cause death. Call your healthcare provider right away if you have:

- fever
- rash
- swelling of your face
- weakness, fatigue
- severe muscle pain

- swollen lymph glands
- unusual bruising or bleeding
- yellowing of your skin or the white part of your eyes

- ZONISADE may cause decreased sweating and increased body temperature (fever).People, especially children, should be watched for signs of decreased sweating and fever, especially in hot temperatures. Some people may need to be hospitalized for this condition. If you have decreased sweating with or without a fever, call your healthcare provider right away.
- ZONISADE may cause eye problems.Serious eye problems include:
  - any sudden decrease in vision with or without eye pain and redness
  - a blockage of fluid in the eye causing increased pressure in the eye (secondary angle closure glaucoma)

These eye problems can lead to permanent loss of vision if not treated.

Call your healthcare provider right away if you have any new eye symptoms, including any new problems with your vision.

- Like other antiepileptic drugs, ZONISADE may cause suicidal thoughts or actions in a very small number of people, about 1 in 500.

Call a healthcare provider right away if you have any of these symptoms, especially if they are new, worse, or worry you:

- thoughts about suicide or dying
- new or worse depression
- feeling agitated or restless
- trouble sleeping (insomnia)
- acting aggressive, being angry, or violent
- an extreme increase in activity and talking (mania)

- attempt to commit suicide
- new or worse anxiety
- panic attacks
- new or worse irritability
- acting on dangerous impulses
- other unusual changes in behavior or mood

Suicidal thoughts or actions can be caused by things other than medicines. If you have suicidal thoughts or actions, your healthcare provider may check for other causes.

How can I watch for early symptoms of suicidal thoughts and actions?

- Pay attention to any changes, especially sudden changes, in mood, behaviors, thoughts, or feelings.
- Keep all follow-up visits with your healthcare provider as scheduled.
- Call your healthcare provider between visits as needed, especially if you are worried about symptoms.

Do not stop ZONISADE without first talking to a healthcare provider.

- Stopping ZONISADE suddenly can cause serious problems.
- Stopping a seizure medicine suddenly in a patient who has epilepsy can cause seizures that will not stop (status epilepticus).
- ZONISADE can increase the level of acid in your blood (metabolic acidosis).If left untreated, metabolic acidosis can cause brittle or soft bones (osteoporosis, osteomalacia, osteopenia), kidney stones and can slow the rate of growth in children. Metabolic acidosis can happen with or without symptoms. Call your healthcare provider right away if you have any of these symptoms:

- fast breathing
- feel tired
- feel changes in heartbeat

- not feel hungry (loss of appetite)
- have trouble thinking clearly

Your healthcare provider should do a blood test to measure the level of acid in your blood before and during your treatment with ZONISADE.

- ZONISADE may cause problems with thinking and alertness.ZONISADE may affect how you think and cause confusion, problems with concentration, attention, memory, or speech. ZONISADE may cause depression or psychotic symptoms (such as seeing or hearing things that are really not there), tiredness, and sleepiness.
  ZONISADE can have other serious side effects. For more information ask your healthcare provider or pharmacist. Tell your healthcare provider if you have any side effect that bothers you. Be sure to read the section " What are the possible side effects of ZONISADE?”.

What is ZONISADE?

- ZONISADE is a prescription medicine that is used with other medicines to treat partial seizures in adults and children 16 years of age and older.
- It is not known if ZONISADE is safe and effective in children under 16 years of age.

Do not take ZONISADE if you:

- are allergic to sulfonamides or zonisamide.

Before taking ZONISADE, tell your healthcare provider about all your medical conditions, including if you:

- have or have had depression, mood problems or suicidal thoughts or behavior.
- have kidney problems.
- have liver problems.
- have a history of metabolic acidosis (too much acid in your blood).
- have weak, brittle bones or soft bones (osteomalacia, rickets, osteopenia, or osteoporosis).
- have a growth problem.
- are on a diet high in fat called a ketogenic diet.
- have diarrhea.
- have high blood levels of ammonia.
- are pregnant or plan to become pregnant. ZONISADE may harm your unborn baby. Women who can become pregnant should use effective birth control. Tell your healthcare provider right away if you become pregnant or think you may be pregnant while taking ZONISADE. You and your healthcare provider should decide if you should take ZONISADE while you are pregnant.
  There is pregnancy registry for women who are exposed to ZONISADE during pregnancy. If you become pregnant while taking ZONISADE, talk to your healthcare provider about registering with the North American Antiepileptic Drug Pregnancy Registry. You can enroll in this registry by calling 1-888-233-2334. The purpose of this registry is to collect information about the safety of antiepileptic drugs during pregnancy.
- are breastfeeding or plan to breastfeed. ZONISADE can pass into your breast milk. It is not known if ZONISADE in your breast milk can harm your baby. Talk to your healthcare provider about the best way to feed your baby if you take ZONISADE. If you breastfeed while taking ZONISADE, check your baby and call your healthcare provider right away if your baby has increased sleepiness, decreased hunger, or elevated body temperature.

Tell your healthcare provider about all the medicines you take, including prescription and over-the- counter medicines, vitamins, and herbal supplements.

How should I take ZONISADE?

- Take ZONISADE exactly as your healthcare provider tells you to take it.
- ZONISADE is for oral use only.
- Your healthcare prescriber may change your dose. Do notchange your dose without talking to your healthcare provider.
- Your pharmacist will provide a measuring device and instructions for measuring the correct dose. Do not use a household teaspoon.
- Take ZONISADE 1 or 2 times each day, with or without food.
- Shake ZONISADE well each time before taking.
- If you take too much ZONISADE, call your local Poison Control Center or go to the nearest emergency room right away.
- Do notstop taking ZONISADE without talking to your healthcare provider. Stopping ZONISADE suddenly can cause serious problems. If you have epilepsy and you stop taking ZONISADE suddenly, you may have an increase in seizures, including seizures that will not stop (status epilepticus).

What should I avoid while taking ZONISADE?

- You should not drink alcohol or take other drugs that make you sleepy or dizzy while taking ZONISADE until you talk to your health care provider. ZONISADE taken with alcohol or drugs that cause sleepiness or dizziness may make your sleepiness or dizziness worse.
- Do not drive a car or operate machinery until you know how ZONISADE affects you. ZONISADE can slow your thinking and motor skills.

What are the possible side effects of ZONISADE?
ZONISADE can cause serious side effects including:

See "What is the most important information I should know about ZONISADE?"

- high blood ammonia levels.High ammonia in the blood can affect your mental status, slow your alertness, make you feel tired, or cause vomiting. Call your healthcare provider right away if you develop unexplained tiredness, vomiting, slow alertness or changes in your mental status.
- kidney stones.Drink plenty of fluids while you take ZONISADE to decrease your chances of getting kidney stones. Call your healthcare provider right away if you get back pain, stomach pain, or blood in your urine.
- decrease in kidney function.ZONISADE may cause a decrease in kidney function. Your healthcare provider should do a blood test to measure your kidney function before and during treatment with ZONISADE.

The most common side effects of ZONISADE include:

- drowsiness
- dizziness
- agitation or irritability

- loss of appetite
- trouble with walking and coordination
- difficulty with memory or concentration

These are not all of the possible side effects of ZONISADE. Call your doctor for medical advice about side effects. You may report side effects to FDA at 1-800-FDA-1088.

You may also report side effects to Azurity Pharmaceuticals, Inc. at 1-855-379-0383.

How should I store ZONISADE?

- Store ZONISADE at room temperature between 68°F to 77°F (20°C to 25°C).
- Protect ZONISADE from light.
- Throw away (discard) any unused ZONISADE 30 days after first opening the bottle.

Keep ZONISADE and all medicines out of the reach of children.

General Information about the safe and effective use of ZONISADE.

Medicines are sometimes prescribed for purposes other than those listed in a Medication Guide. Do not use ZONISADE for a condition for which it was not prescribed. Do not give ZONISADE to other people, even if they have the same symptoms that you have. It may harm them. You can ask your pharmacist or healthcare provider for information about ZONISADE that is written for health professionals.

What are the ingredients in ZONISADE?
Active ingredient:zonisamide

Inactive ingredients:carboxymethylcellulose sodium, citric acid monohydrate, microcrystalline cellulose, purified water, sodium benzoate, strawberry flavor, sucralose, trisodium citrate dihydrate, and xanthan gum.

Manufactured for:

Azurity Pharmaceuticals, Inc.
Wilmington, MA 01887 USA

This Medication Guide has been approved by the U.S. Food and Drug Administration.

Approved: 03/2023

PRINCIPAL DISPLAY PANEL - Carton Label

NDC 52652-8001-1

ZONISADE®
(zonisamide
oral suspension)

100 mg/5 mL

FOR ORAL USE ONLY
SHAKE WELL BEFORE USE

150 mL Rx Only

ATTENTION PHARMACIST:
Dispense Medication Guide to each
patient. Medication Guide available at:
zonisade.com/medication-guide.pdf

azurity®
pharmaceuticals